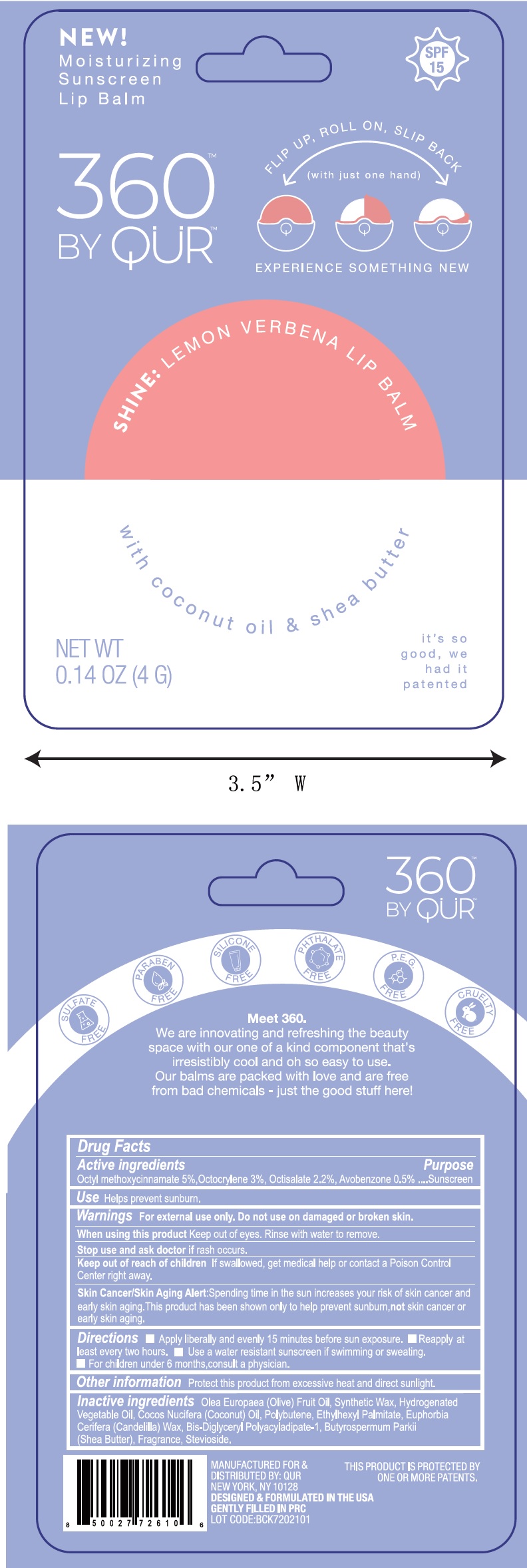 DRUG LABEL: 360 by QUR Lemon Verbena lip balm
NDC: 81761-113 | Form: STICK
Manufacturer: Qur, Inc
Category: otc | Type: HUMAN OTC DRUG LABEL
Date: 20250123

ACTIVE INGREDIENTS: OCTINOXATE 50 mg/1 g; OCTOCRYLENE 30 mg/1 g; OCTISALATE 22 mg/1 g; AVOBENZONE 5 mg/1 g
INACTIVE INGREDIENTS: COCONUT OIL; POLYBUTENE (1400 MW); ETHYLHEXYL PALMITATE; CANDELILLA WAX; BIS-DIGLYCERYL POLYACYLADIPATE-1; SHEA BUTTER; STEVIOSIDE; OLIVE OIL

360 by QUR Lemon Verbena lip balm

Active ingredients

Octyl methoxycinnamate 5%, Octocrylene 3%, Octisalate 2.2%, Avobenzone 0.5%

Purpose

Sunscreen

Use

Helps prevent sunburn.

Warnings

For external use only.

Do not use

on damaged or broken skin.

When using this product

Keep out of eyes. Rinse with water to remove.

Stop use and ask a doctor if

rash occurs.

Keep out of the reach of children

If swallowed, get medical help or contact a Poison Control Center right away.

Spending time in the sun increase your risk of skin cancer and early skin aging. This product has been shown only to help prevent sunburn, not skin cancer or early skin aging. Skin Cancer/Skin Aging Alert:

Directions

- Apply liberally and evenly 15 minutes before sun exposure.
- Reapply at least every two hours.
- Use a water resistant sunscreen if swimming or sweating.
- For children under 6 months, consult a physician.

Other information

Protect this product from excessive heat and direct sunlight.

Inactive ingredients

Olea Europaea (Olive) Fruit Oil, Synthetic Wax, Hydrogenated Vegetable Oil, Cocos Nucifera (Coconut) Oil, Polybutene, Ethylhexyl Palmitate, Euphorbia Cerifera (Candelilla) wax, Bis-Diglyceryl Polyacyladipate-1, Butyrospermum Parkii (Shea Butter), Fragrance, Stevioside.